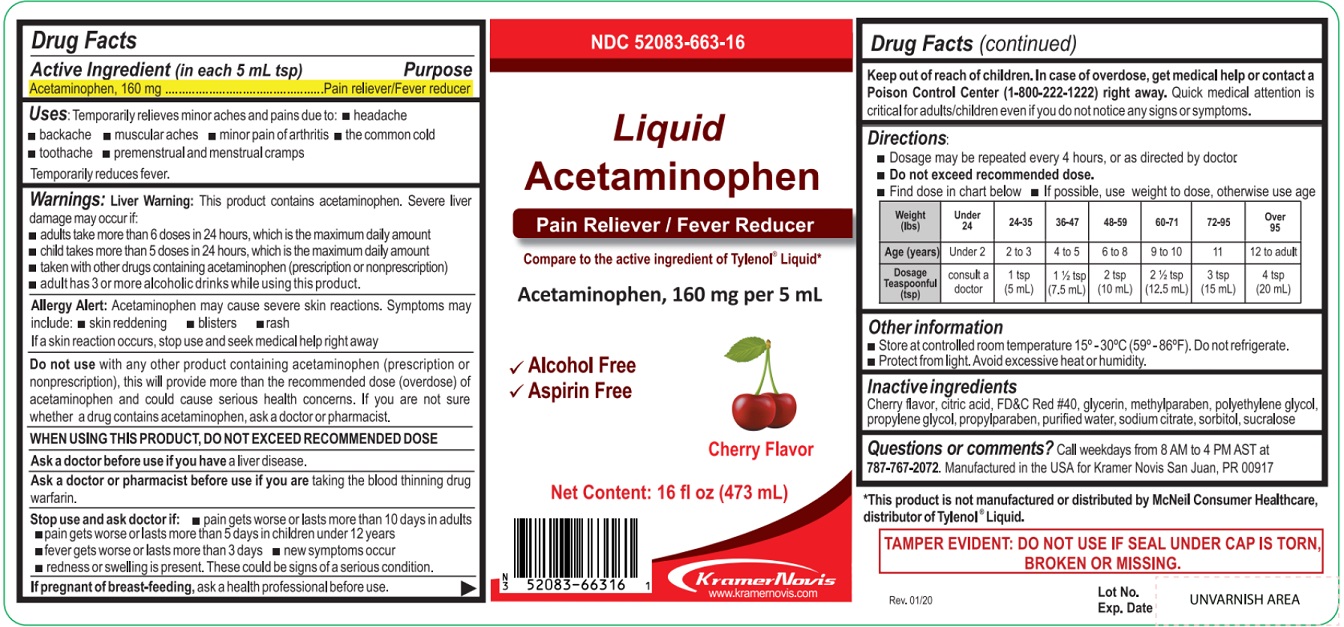 DRUG LABEL: Liquid Acetaminophen
NDC: 52083-663 | Form: LIQUID
Manufacturer: KRAMER NOVIS
Category: otc | Type: HUMAN OTC DRUG LABEL
Date: 20200302

ACTIVE INGREDIENTS: ACETAMINOPHEN 160 mg/5 mL
INACTIVE INGREDIENTS: CITRIC ACID MONOHYDRATE; FD&C RED NO. 40; GLYCERIN; METHYLPARABEN; POLYETHYLENE GLYCOL, UNSPECIFIED; PROPYLENE GLYCOL; PROPYLPARABEN; WATER; SODIUM CITRATE, UNSPECIFIED FORM; SORBITOL; SUCRALOSE

Liquid Acetaminophen

Active ingredient (in each 5 mL tsp)

Acetaminophen, 160 mg

Purpose

Pain reliever/Fever reducer

Uses:

Temporarily relieves of minor aches and pains due to • headache • backache • muscular aches • minor pain of arthritis • the common cold • toothache • premenestrual and menstrual cramps

Temporarily reduces fever.

Warnings:

Liver warning: This product contains acetaminophen. Severe liver damage may occur if:

• adults take more than 6 doses in 24 hours, which is the maximum daily amount

• child takes more than 5 doses in 24 hours, which is the maximum daily amount

• taken with other drugs containing acetaminophen (prescription or nonprescription)

• adults has 3 or more alcoholic drinks while using this product

Allergy alert: Acetaminophen may cause severe skin reactions. Symptoms may include: • skin reddening • blisters • rash

If a skin reaction occurs, stop use and seek medical help right away

Do not use with any other product containing acetaminophen (prescription or nonprescription), this will provide more than the recommended dose (overdose) of acetaminophen and could cause serious health concerns. If you are not sure whether a drug contains acetaminophen, ask a doctor or pharmacist.

WHEN USING THIS PRODUCT, DO NOT EXCEED RECOMMENDED DOSE

Ask a doctor before use if you have a liver disease.

Ask a doctor or pharmacist before use if you are taking the blood thinning drug warfarin.

Stop use and ask a doctor if • pain gets worse or lasts more than 10 days in adults

• pain gets worse or lasts more than 5 days in children under 12 years

• fever gets worse or lasts more than 3 days • new symptoms occur

• redness or swelling is present. These could be signs of a serious condition.

If pregnant or breast-feeding, ask a health professional before use.

Keep out of reach of children. In case of overdose, get medical help or contact a Poison Control Center (1-800-222-1222) right away. Quick medical attention is critical for adults/children even if you do not notice any signs or symptoms.

Directions

Dosage may be repeated every 4 hours, or as directed by doctor.

Do not exceed recommended dose.

Find dose in chart below. If possible, use weight to dose, otherwise use age.

Weight; (lbs) | Under 24 | 24-35 | 36-47 | 48-59 | 60-71 | 72-95 | Over 95
Age (years) | Under 2 | 2 to 3 | 4 to 5 | 6 to 8 | 9 to 10 | 11 | 12 to adult
Dosage; teaspoonful; (tsp) | consult a doctor | 1 tsp; (5 mL) | 1 1/2 tsp (7.5 mL) | 2 tsp (10 mL) | 2 1/2 tsp (12.5 mL) | 3 tsp (15 mL) | 4 tsp (20 mL)

Other information

• Store at controlled room tempearature 15°-30°C (59°-86°F). Do not refrigerate.

• Protect from light. Avoid excessive heat or humidity.

Inactive ingredients

Cherry flavor, citric acid, FD&C Red #40, glycerin, methylparaben, polyethylene glycol, propylene glycol, propylparaben, purified water, sodium citrate, sorbitol, sucralose

Questions or comments?

Call weekdays from 8 AM to 4 PM AST at 787-767-2072.

Manufactured in the USA for Kramer Novis, San Juan, PR 00917

Compare to the active ingredient of Tylenol® Liquid*

√ Alcohol Free

√ Aspirin Free

Cherry Flavor

*This product is not manufactured or distributed by McNeil Consumer Healthcare, distributor of Tylenol® Liquid.

TAMPER EVIDENT: DO NOT USE IF SEAL UNDER CAP IS TORN, BROKEN OR MISSING.

www.kramernovis.com